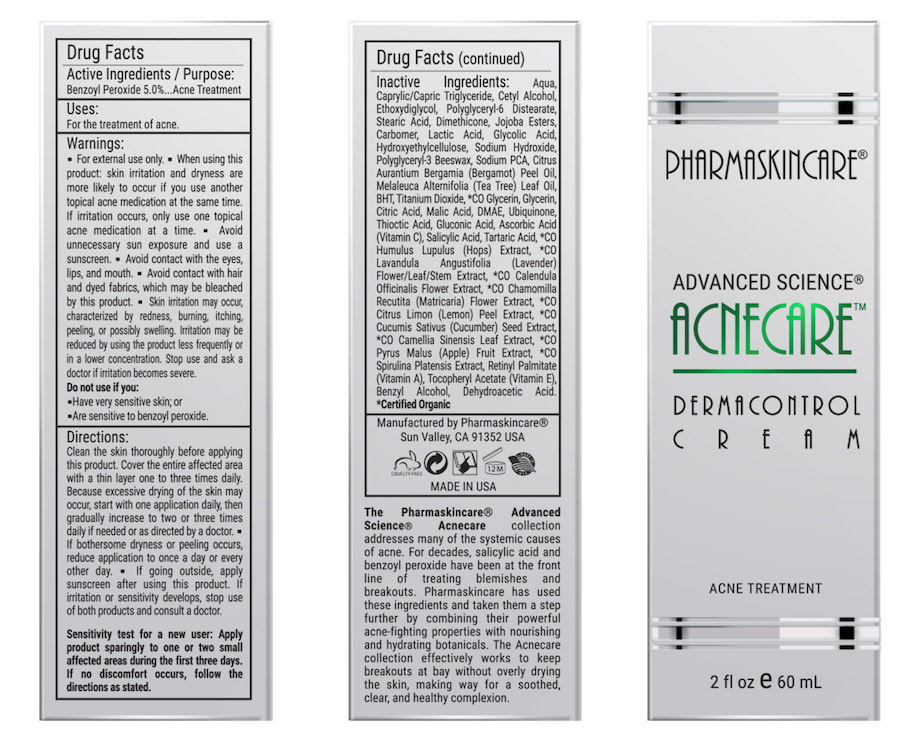 DRUG LABEL: Acnecare Dermacontrol Cream
NDC: 68062-8090 | Form: LIQUID
Manufacturer: Spa de Soleil
Category: otc | Type: HUMAN OTC DRUG LABEL
Date: 20260121

ACTIVE INGREDIENTS: BENZOYL PEROXIDE 3 mg/60 mL
INACTIVE INGREDIENTS: CETYL ALCOHOL; WATER; ETHOXYDIGLYCOL OLEATE; CAPRYLIC/CAPRIC ACID

Acnecare Dermacontrol Cream

Active ingredient Purpose

Benzoyl Peroxide (5%)..........Acne Treatment

Purpose

Acne Treatment

INDICATIONS AND USAGE

For treatment of acne

Warnings

For external use only

Avoid contact with eyes. If contact occurs, rinse thoroughly with water.

If swallowed, get medical help or contact a Poison Control Center right away. If excessive skin irritation develops or increases, discontinue use and consult a doctor. Keep out of reach of children.

Keep out of reach of children. In case of accidental ingestion, get medical help or contact a Poison Control Center right away.

When using this product

• Skin irritation and dryness is more likely to occur if you use another topical acne medication while using this product. If irritation occurs, use only one topical acne medication at a time.

Directions:

Clean the skin thoroughly before applying this product. Cover the entire affected area with a thin layer one to three times daily. Because excessive drying of the skin may occur, start with one application daily, then gradually increase to two or three times daily if needed or as directed by a doctor. . If bothersome dryness or peeling occurs, reduce application to once a day or every other day. . If going outside, apply sunscreen after using this product. If irritation or sensitivity develops, stop use of both products and consult a doctor.

Sensitivity test for a new user: Apply product sparingly to one or two small affected areas during the first three days. If no discomfort occurs, follow the directions as stated.

INACTIVE INGREDIENT

Other Ingredients:

Aqua, Caprylic/Capric Triglyceride, Cetyl Alcohol, Ethoxydiglycol, Polyglyceryl-6 Distearate, Stearic Acid, Dimethicone, Jojoba Esters, Carbomer, Lactic Acid, Glycolic Acid, Hydroxyethylcellulose, Sodium Hydroxide, Polyglyceryl-3 Beeswax, Sodium PCA, Citrus Aurantium Bergamia (Bergamot) Peel Oil, Melaleuca Alternifolia (Tea Tree) Leaf Oil, BHT, Titanium Dioxide, *CO Glycerin, Glycerin, Citric Acid, Malic Acid, DMAE, Ubiquinone, Thioctic Acid, Gluconic Acid, Ascorbic Acid (Vitamin C), Salicylic Acid, Tartaric Acid, *CO Humulus Lupulus (Hops) Extract, *CO Lavandula Angustifolia (Lavender) Flower/Leaf/Stem Extract, *CO Calendula Officinalis Flower Extract, *CO Chamomilla Recutita (Matricaria) Flower Extract, *CO Citrus Limon (Lemon) Peel Extract, *CO Cucumis Sativus (Cucumber) Seed Extract, *CO Camellia Sinensis Leaf Extract, *CO Pyrus Malus (Apple) Fruit Extract, *CO Spirulina Platensis Extract, Retinyl Palmitate (Vitamin A), Tocopheryl Acetate (Vitamin E), Benzyl Alcohol, Dehydroacetic Acid. *Certified Organic